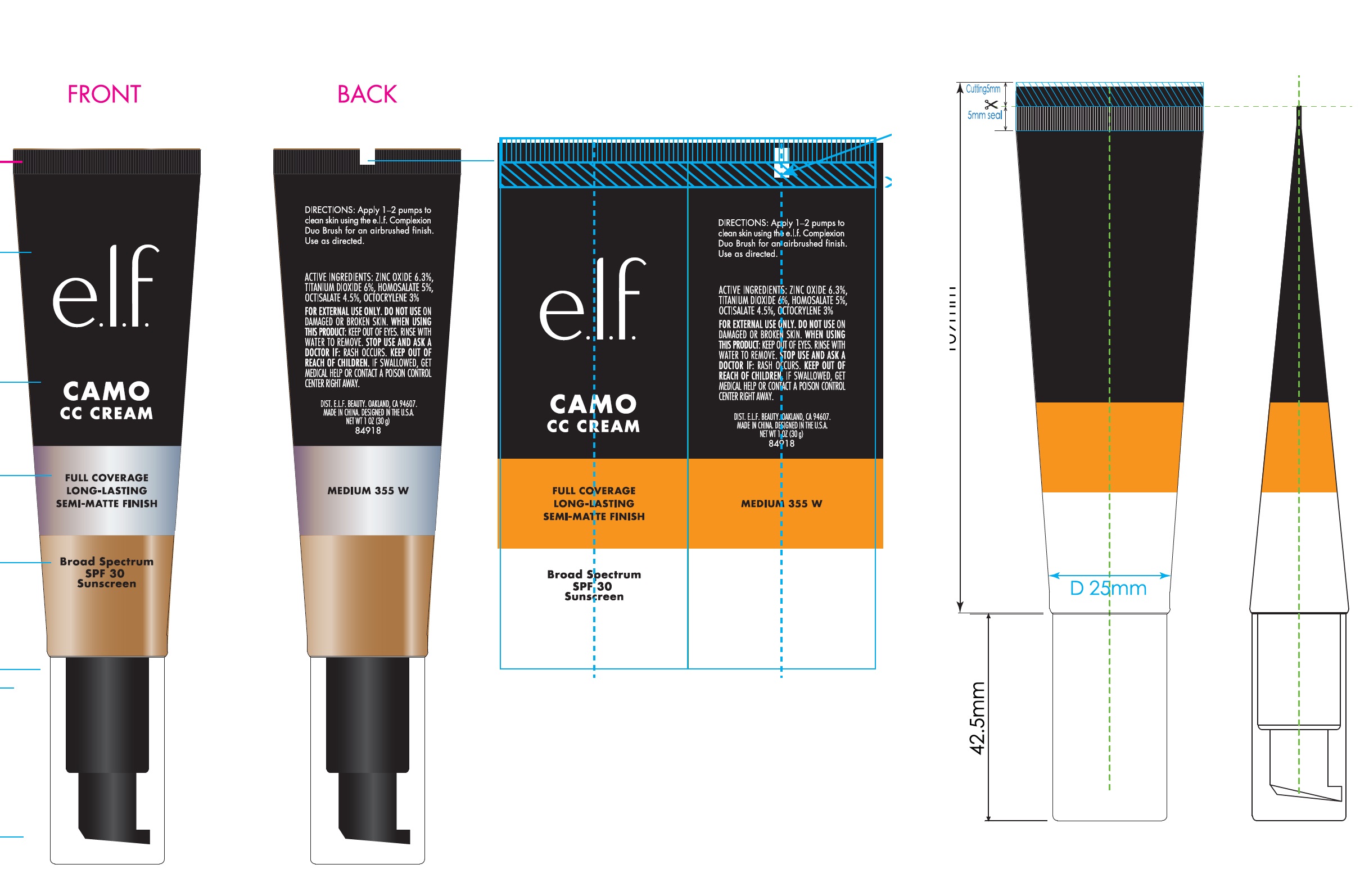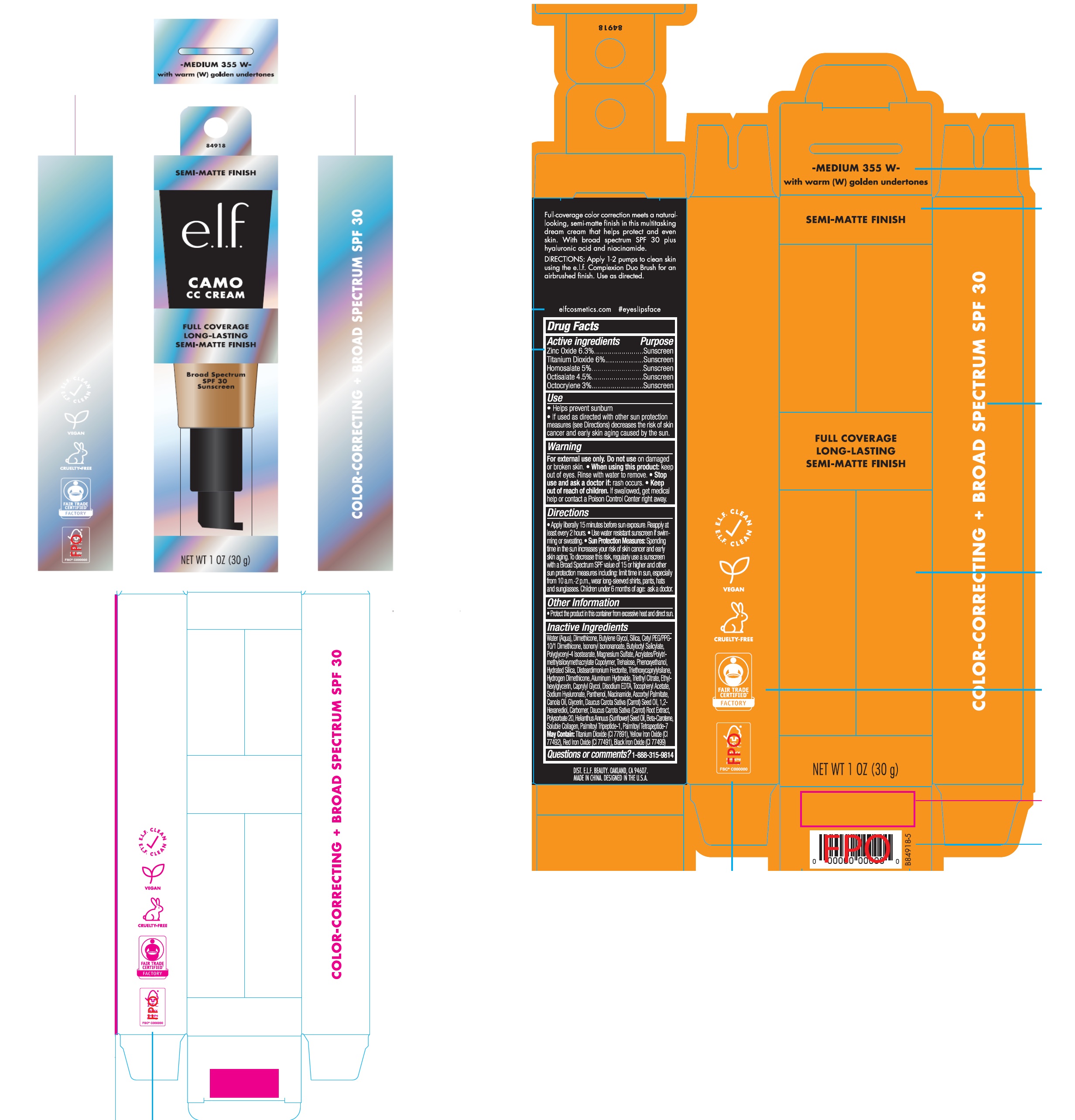 DRUG LABEL: e.l.f Camo Semi-Matte CC SPF 30 Medium 355 W
NDC: 76354-518 | Form: CREAM
Manufacturer: e.l.f. Cosmetics, Inc.
Category: otc | Type: HUMAN OTC DRUG LABEL
Date: 20251107

ACTIVE INGREDIENTS: ZINC OXIDE 63 mg/1 g; TITANIUM DIOXIDE 60 mg/1 g; HOMOSALATE 50 mg/1 g; OCTISALATE 45 mg/1 g; OCTOCRYLENE 30 mg/1 g
INACTIVE INGREDIENTS: WATER; DIMETHICONE; BUTYLENE GLYCOL; SILICON DIOXIDE; ISONONYL ISONONANOATE; BUTYLOCTYL SALICYLATE; POLYGLYCERYL-4 ISOSTEARATE; MAGNESIUM SULFATE, UNSPECIFIED FORM; TREHALOSE; PHENOXYETHANOL; HYDRATED SILICA; DISTEARDIMONIUM HECTORITE; TRIETHOXYCAPRYLYLSILANE; ALUMINUM HYDROXIDE; TRIETHYL CITRATE; ETHYLHEXYLGLYCERIN; CAPRYLYL GLYCOL; EDETATE DISODIUM; .ALPHA.-TOCOPHEROL ACETATE; HYALURONATE SODIUM; PANTHENOL; NIACINAMIDE; ASCORBYL PALMITATE; CANOLA OIL; GLYCERIN; CARROT SEED OIL; 1,2-HEXANEDIOL; CARBOMER HOMOPOLYMER, UNSPECIFIED TYPE; POLYSORBATE 20; SUNFLOWER OIL; BETA CAROTENE; PALMITOYL TRIPEPTIDE-1; PALMITOYL TETRAPEPTIDE-7

e.l.f Camo Semi-Matte CC Cream SPF 30 Medium 355 W

Active ingredients

Zinc Oxide 6.3%

Titanium Dioxide 6%

Homosalate 5%

Octisalate 4.5%

Octocrylene 3%

Purpose

Sunscreen

Use

- Helps prevent sunburn
- If used as directed with other sun protection measures (see Directions) decreases the risk of skin cancer and early skin aging caused by the sun.

Warning

For external use only.

Do not use

on damaged or broken skin.

• When using this product:

keep out of eyes. Rinse with water to remove.

• Stop use and ask a doctor if:

rash occurs.

• Keep out of reach of children.

If swallowed, get medical help or contact a Poison Control Center right away.

Directions

• Apply liberally 15 minutes before sun exposure. Reapply at least every 2 hours. • Use water resistant sunscreen if swimming or sweating. • Sun Protection Measures: Spending time in the sun increases your risk of skin cancer and early skin aging. To decrease this risk, regularly use a sunscreen with a Broad Spectrum SPF value of 15 or higher and other sun protection measures including: limit time in sun, especially from 10 a.m. - 2 p.m., wear long-sleeved shirts, pants, hats and sunglasses. Children under 6 months of age: ask a doctor.

Other Information

- Protect the product in this container from excessive heat and direct sun.

Inactive Ingredients

Water (Aqua), Dimethicone, Butylene Glycol, Silica, Cetyl PEG/PPG-10/1 Dimethicone, Isononyl Isononanoate, Butyloctyl Salicylate, Polyglyceryl-4 Isostearate, Magnesium Sulfate, Acrylates/Polytrimethylsiloxymethacrylate Copolymer, Trehalose, Phenoxyethanol, Hydrated Silica, Disteardimonium Hectorite, Triethoxycaprylylsilane, Hydrogen Dimethicone, Aluminum Hydroxide, Triethyl Citrate, Ethylhexylglycerin, Caprylyl Glycol, Disodium EDTA, Tocopheryl Acetate, Sodium Hyaluronate, Panthenol, Niacinamide, Ascorbyl Palmitate, Canola Oil, Glycerin, Daucus Carota Sativa (Carrot) Seed Oil, 1,2-Hexanediol, Carbomer, Daucus Carota Sativa(Carrot) Root Extract, Polysorbate 20, Helianthus Annuus (Sunflower) Seed Oil, Beta-Carotene, Soluble Collagen, Palmitoyl Tripeptide-1, Palmitoyl Tetrapeptide-7
May Contain:Titanium Dioxide (CI 77891), Yellow Iron Oxide (CI 77492), Red Iron Oxide (CI 77491), Black Iron Oxide (CI 77499)

Questions or comments?

1-888-315-9814